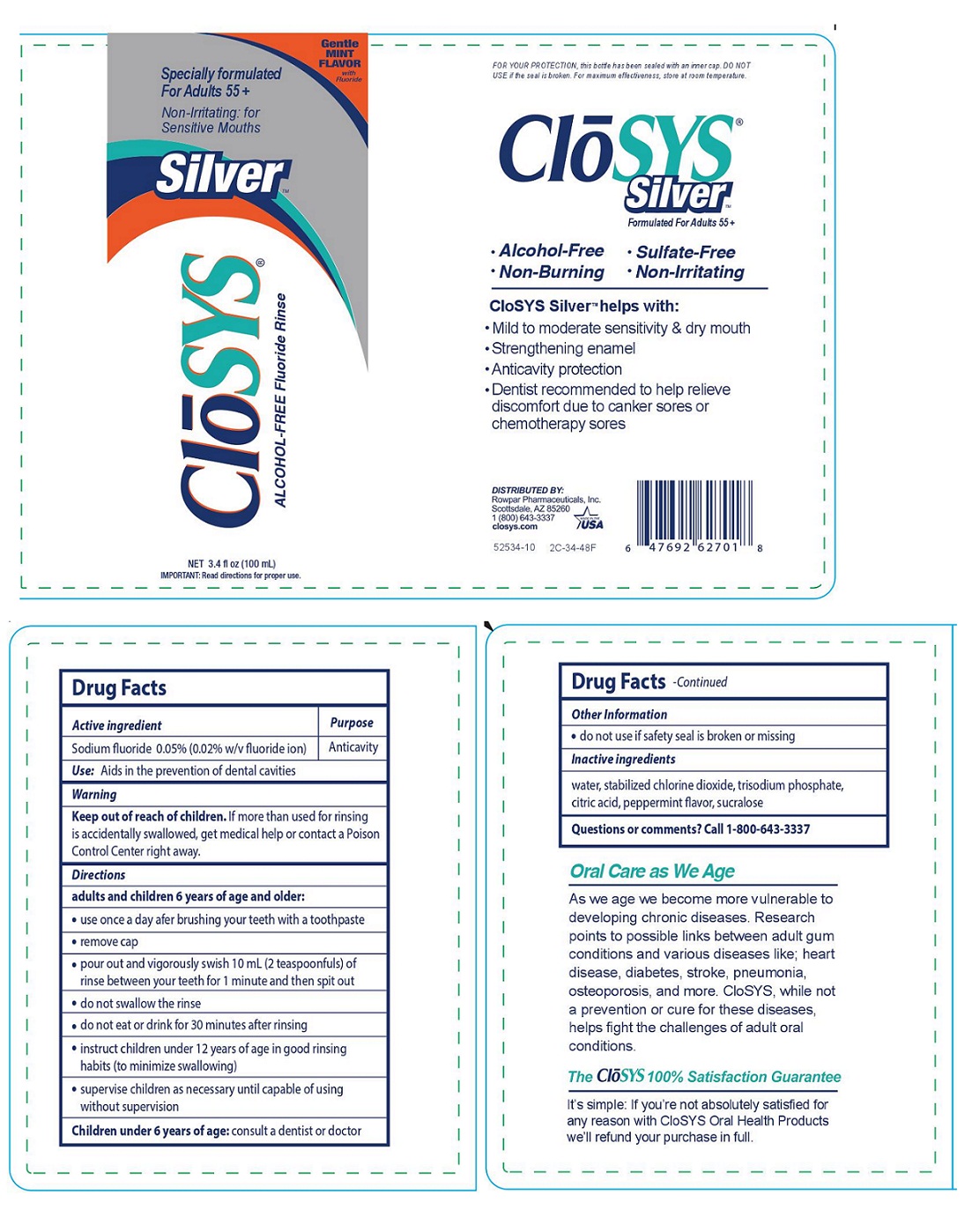 DRUG LABEL: CloSYS
NDC: 58578-1234 | Form: RINSE
Manufacturer: Rowpar Pharmaceuticals, Inc.
Category: otc | Type: HUMAN OTC DRUG LABEL
Date: 20160220

ACTIVE INGREDIENTS: SODIUM FLUORIDE 0.05 g/100 mL
INACTIVE INGREDIENTS: WATER; CHLORINE DIOXIDE; SODIUM PHOSPHATE, TRIBASIC, DODECAHYDRATE; ANHYDROUS CITRIC ACID; PEPPERMINT; SUCRALOSE

CloSYS® Silver ALCOHOL-FREE Fluoride Rinse

Active ingredient

Sodium fluroide 0.05% (0.02% w/v fluoride ion)

Purpose

Anticavity

INDICATIONS AND USAGE

Use: Aids in the prevention of dental cavities

Keep out of reach of children. If more than used for rinsing is accidentally swallowed, get medical help or contact a Poison Control Center right away.

Directions

adults and children 6 years of age and older:

- use once a day after brushing your teeth with a toothpaste
- remove cap
- pour out and vigorously swish 10 mL (2 teaspoonfuls) of rinse between your teeth for 1 minute and then spit out
- do not swallow the rinse
- do not eat or drink for 30 minutes after rinsing
- instruct children under 12 years of age in good rinsing habits (to minimize swallowing)
- supervise children as necessary until capable of using without supervision

Children under 6 years of age: consult a dentist or doctor

Inactive ingredients

water, stabilized chlorine dioxide, trisodium phosphate, citric acid, peppermint flavor, sucralose

Other Information

- do not use if safety seal is broken or missing

Questions or comments? Call 1-800-643-3337

Specially formulated For Adults 55+

Non-Irritating: for Sensitive Mouths

•Alcohol-Free • Sulfate-Free

• Non-Burning • Non-Irritating

Gentle MINT FLAVOR with Fluoride

CloSYS SilverTM helps with:

• Mild to moderate sensitivity & dry mouth
• Strengthening enamel
• Anticavity protection
• Dentist recommended to help relieve discomfort due to canker sores or chemotherapy sores

FOR YOUR PROTECTION, this bottle has been sealed with an inner cap. DO NOT USE if the seal is broken. For maximum effectiveness, store at room temperature.

Oral Care as We Age

As we age we become more vulnerable to developing chronic diseases. Research points to possible links between adult gum conditions and various diseases like; heart disease, diabetes, stroke, pneumonia, osteoporosis, and more. CloSYS, while not a prevention or cure for these diseases, helps fight the challenges of adult oral conditions.

The CloSYS 100% Satisfaction Guarantee

It’s simple: If you’re not absolutely satisfied for any reason with CloSYS Oral Health Products we’ll refund your purchase in full.

DISTRIBUTED BY:

Rowpar Pharmaceuticals, Inc.
Scottsdale, AZ 85260
1 (800) 643-3337
closys.com